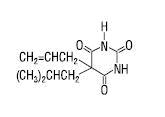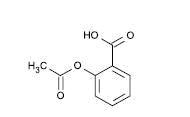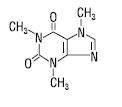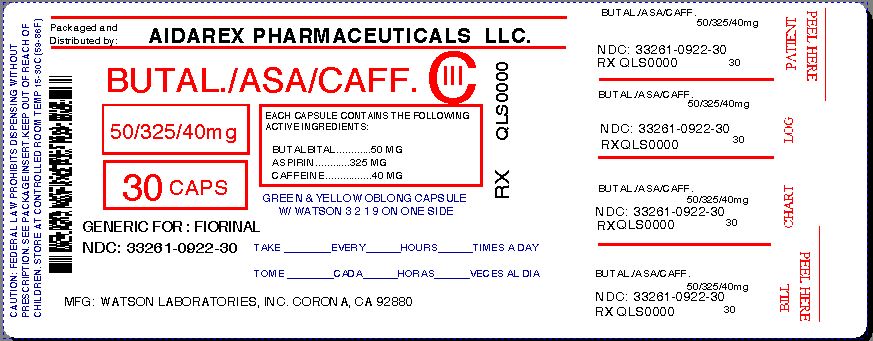 DRUG LABEL: Butalbital, Aspirin, and Caffeine
NDC: 33261-922 | Form: CAPSULE
Manufacturer: Aidarex Pharmaceuticals LLC
Category: prescription | Type: HUMAN PRESCRIPTION DRUG LABEL
Date: 20131223
DEA Schedule: CIII

ACTIVE INGREDIENTS: BUTALBITAL 50 mg/1 1; ASPIRIN 325 mg/1 1; CAFFEINE 40 mg/1 1
INACTIVE INGREDIENTS: CELLULOSE, MICROCRYSTALLINE; STARCH, CORN; TALC; D&C YELLOW NO. 10; FD&C GREEN NO. 3; GELATIN; FERRIC OXIDE RED

Butalbital, Aspirin, and Caffeine Capsules, USP C-III
Revised: June 2009
Rx only
1901100609

DESCRIPTION

Butalbital, Aspirin, and Caffeine Capsules, USP is supplied in capsule form for oral administration.

Each capsule contains the following active ingredients:

butalbital, USP . . . . . . . . . . . . . | 50 mg
aspirin, USP. . . . . . . . . . . . . . . . | 325 mg
caffeine, USP . . . . . . . . . . . . . . | 40 mg

Butalbital (5-allyl-5-isobutylbarbituric acid) is a short- to intermediate-acting barbiturate. It has the following structural formula:

C11H16N2O3 molecular weight 224.26

Aspirin (benzoic acid, 2-(acetyloxy)-) is an analgesic, antipyretic, and anti-inflammatory. It has the following structural formula:

C9H8O4 molecular weight 180.16

Caffeine (1,3,7-trimethylxanthine) is a central nervous system stimulant. It has the following structural formula:

C8H10N4O2 molecular weight 194.19

Inactive Ingredients: microcrystalline cellulose, pregelatinized starch, and talc. Gelatin capsules contain D&C Yellow No. 10, FD&C Green No. 3, and gelatin. The capsules are printed with edible ink containing red iron oxide.

CLINICAL PHARMACOLOGY

Pharmacologically, Butalbital, Aspirin, and Caffeine Capsules, USP combines the analgesic properties of aspirin with the anxiolytic and muscle relaxant properties of butalbital.

The clinical effectiveness of butalbital, aspirin, and caffeine capsules in tension headache has been established in double-blind, placebo-controlled, multi-clinic trials. A factorial design study compared butalbital, aspirin, and caffeine capsules with each of its major components. This study demonstrated that each component contributes to the efficacy of butalbital, aspirin, and caffeine capsules in the treatment of the target symptoms of tension headache (headache pain, psychic tension, and muscle contraction in the head, neck, and shoulder region). For each symptom and the symptom complex as a whole, butalbital, aspirin, and caffeine capsules was shown to have significantly superior clinical effects to either component alone.

Pharmacokinetics

The behavior of the individual components is described below.

Aspirin
The systemic availability of aspirin after an oral dose is highly dependent on the dosage form, the presence of food, the gastric emptying time, gastric pH, antacids, buffering agents, and particle size. These factors affect not necessarily the extent of absorption of total salicylates but more the stability of aspirin prior to absorption.

During the absorption process and after absorption, aspirin is mainly hydrolyzed to salicylic acid and distributed to all body tissues and fluids, including fetal tissues, breast milk, and the central nervous system (CNS). Highest concentrations are found in plasma, liver, renal cortex, heart, and lung. In plasma, about 50%-80% of the salicylic acid and its metabolites are loosely bound to plasma proteins.

The clearance of total salicylates is subject to saturable kinetics; however, first-order elimination kinetics are still a good approximation for doses up to 650 mg. The plasma half-life for aspirin is about 12 minutes and for salicylic acid and/or total salicylates is about 3 hours.

The elimination of therapeutic doses is through the kidneys either as salicylic acid or other biotransformation products. The renal clearance is greatly augmented by an alkaline urine as is produced by concurrent administration of sodium bicarbonate or potassium citrate.

The biotransformation of aspirin occurs primarily in the hepatocytes. The major metabolites are salicyluric acid (75%), the phenolic and acyl glucuronides of salicylate (15%), and gentisic and gentisuric acid (1%). The bioavailability of the aspirin component of Butalbital, Aspirin, and Caffeine Capsules, USP is equivalent to that of a solution except for a slower rate of absorption. A peak concentration of 8.8 mcg/mL was obtained at 40 minutes after a 650 mg dose.

See OVERDOSAGE for toxicity information.

Butalbital
Butalbital is well absorbed from the gastrointestinal tract and is expected to distribute to most of the tissues in the body. Barbiturates, in general, may appear in breast milk and readily cross the placental barrier. They are bound to plasma and tissue proteins to a varying degree and binding increases directly as a function of lipid solubility.

Elimination of butalbital is primarily via the kidney (59%-88% of the dose) as unchanged drug or metabolites. The plasma half-life is about 35 hours. Urinary excretion products included parent drug (about 3.6% of the dose), 5-isobutyl-5-(2,3-dihydroxypropyl) barbituric acid (about 24% of the dose), 5-allyl-5(3-hydroxy-2-methyl-1-propyl) barbituric acid (about 4.8% of the dose), products with the barbituric acid ring hydrolyzed with excretion of urea (about 14% of the dose), as well as unidentified materials. Of the material excreted in the urine, 32% was conjugated.

The bioavailability of the butalbital component of Butalbital, Aspirin, and Caffeine Capsules, USP is equivalent to that of a solution except for a decrease in the rate of absorption. A peak concentration of 2,020 ng/mL is obtained at about 1.5 hours after a 100 mg dose.

The in vitro plasma protein binding of butalbital is 45% over the concentration range of 0.5-20 mcg/mL. This falls within the range of plasma protein binding (20%-45%) reported with other barbiturates such as phenobarbital, pentobarbital, and secobarbital sodium. The plasma-to-blood concentration ratio was almost unity indicating that there is no preferential distribution of butalbital into either plasma or blood cells.

See OVERDOSAGE for toxicity information.

Caffeine
Like most xanthines, caffeine is rapidly absorbed and distributed in all body tissues and fluids, including the CNS, fetal tissues, and breast milk.

Caffeine is cleared rapidly through metabolism and excretion in the urine. The plasma half-life is about 3 hours. Hepatic biotransformation prior to excretion results in about equal amounts of 1-methylxanthine and 1-methyluric acid. Of the 70% of the dose that has been recovered in the urine, only 3% was unchanged drug.

The bioavailability of the caffeine component for Butalbital, Aspirin, and Caffeine Capsules, USP is equivalent to that of a solution except for a slightly longer time to peak. A peak concentration of 1,660 ng/mL was obtained in less than an hour for an 80 mg dose.

See OVERDOSAGE for toxicity information.

INDICATIONS

Butalbital, Aspirin, and Caffeine Capsules, USP is indicated for the relief of the symptom complex of tension (or muscle contraction) headache. Evidence supporting the efficacy and safety of Butalbital, Aspirin, and Caffeine Capsules, USP in the treatment of multiple recurrent headaches is unavailable. Caution in this regard is required because butalbital is habit-forming and potentially abusable.

CONTRAINDICATIONS

Butalbital, Aspirin, and Caffeine Capsules, USP is contraindicated under the following conditions:

1. Hypersensitivity or intolerance to aspirin, caffeine, or butalbital.
2. Patients with a hemorrhagic diathesis (e.g., hemophilia, hypoprothrombinemia, von Willebrand’s disease, the thrombocytopenias, thrombasthenia and other ill-defined hereditary platelet dysfunctions, severe vitamin K deficiency and severe liver damage).
3. Patients with the syndrome of nasal polyps, angioedema and bronchospastic reactivity to aspirin or other nonsteroidal anti-inflammatory drugs. Anaphylactoid reactions have occurred in such patients.
4. Peptic ulcer or other serious gastrointestinal lesions.
5. Patients with porphyria.

WARNINGS

Therapeutic doses of aspirin can cause anaphylactic shock and other severe allergic reactions. It should be ascertained if the patient is allergic to aspirin, although a specific history of allergy may be lacking.

Significant bleeding can result from aspirin therapy in patients with peptic ulcer or other gastrointestinal lesions, and in patients with bleeding disorders. Aspirin administered preoperatively may prolong the bleeding time. Butalbital is habit-forming and potentially abusable. Consequently, the extended use of Butalbital, Aspirin, and Caffeine Capsules, USP is not recommended. Results from epidemiologic studies indicate an association between aspirin and Reye’s Syndrome. Caution should be used in administering this product to children, including teenagers, with chicken pox or flu.

PRECAUTIONS

General

Butalbital, Aspirin, and Caffeine Capsules, USP should be prescribed with caution for certain special-risk patients such as the elderly or debilitated, and those with severe impairment of renal or hepatic function, coagulation disorders, head injuries, elevated intracranial pressure, acute abdominal conditions, hypothyroidism, urethral stricture, Addison’s disease, or prostatic hypertrophy.

Aspirin should be used with caution in patients on anticoagulant therapy and in patients with underlying hemostatic defects, and extreme caution in the presence of peptic ulcer.

Precautions should be taken when administering salicylates to persons with known allergies. Hypersensitivity to aspirin is particularly likely in patients with nasal polyps, and relatively common in those with asthma.

Information for Patients

Patients should be informed that Butalbital, Aspirin, and Caffeine Capsules, USP contains aspirin and should not be taken by patients with an aspirin allergy.

Butalbital, Aspirin, and Caffeine Capsules, USP may impair the mental and/or physical abilities required for performance of potentially hazardous tasks such as driving a car or operating machinery. Such tasks should be avoided while taking Butalbital, Aspirin, and Caffeine Capsules, USP.

Alcohol and other CNS depressants may produce an additive CNS depression when taken with Butalbital, Aspirin, and Caffeine Capsules, USP and should be avoided.

Butalbital may be habit-forming. Patients should take the drug only for as long as it is prescribed, in the amounts prescribed, and no more frequently than prescribed.

Laboratory Tests

In patients with severe hepatic or renal disease, effects of therapy should be monitored with serial liver and/or renal function tests.

Drug Interactions

The CNS effects of butalbital may be enhanced by monoamine oxidase (MAO) inhibitors.

In patients receiving concomitant corticosteroids and chronic use of aspirin, withdrawal of corticosteroids may result in salicylism because corticosteroids enhance renal clearance of salicylates and their withdrawal is followed by return to normal rates of renal clearance.

Butalbital, Aspirin, and Caffeine Capsules, USP may enhance the effects of:

1. Oral anticoagulants, causing bleeding by inhibiting prothrombin formation in the liver and displacing anticoagulants from plasma protein binding sites.
2. Oral antidiabetic agents and insulin, causing hypoglycemia by contributing an additive effect, if dosage of Butalbital, Aspirin, and Caffeine Capsules, USP exceeds maximum recommended daily dosage.
3. 6-mercaptopurine and methotrexate, causing bone marrow toxicity and blood dyscrasias by displacing these drugs from secondary binding sites, and, in the case of methotrexate, also reducing its excretion.
4. Non-steroidal anti-inflammatory agents, increasing the risk of peptic ulceration and bleeding by contributing additive effects.
5. Other narcotic analgesics, alcohol, general anesthetics, tranquilizers such as chlordiazepoxide, sedative-hypnotics, or other CNS depressants, causing increased CNS depression.

Butalbital, Aspirin, and Caffeine Capsules, USP may diminish the effects of:

Uricosuric agents such as probenecid and sulfinpyrazone, reducing their effectiveness in the treatment of gout. Aspirin competes with these agents for protein binding sites.

Drug/Laboratory Test Interactions

Aspirin: Aspirin may interfere with the following laboratory determinations in blood: serum amylase, fasting blood glucose, cholesterol, protein, serum glutamic-oxaloacetic transaminase (SGOT), uric acid, prothrombin time and bleeding time. Aspirin may interfere with the following laboratory determinations in urine: glucose, 5-hydroxyindoleacetic acid, Gerhardt ketone, vanillylmandelic acid (VMA), uric acid, diacetic acid, and spectrophotometric detection of barbiturates.

Carcinogenesis, Mutagenesis, Impairment of Fertility

Adequate long-term studies have been conducted in mice and rats with aspirin, alone or in combination with other drugs, in which no evidence of carcinogenesis was seen. No adequate studies have been conducted in animals to determine whether aspirin has a potential for mutagenesis or impairment of fertility. No adequate studies have been conducted in animals to determine whether butalbital has a potential for carcinogenesis, mutagenesis, or impairment of fertility.

Usage in Pregnancy

Teratogenic Effects:

Pregnancy Category C. Animal reproduction studies have not been conducted with Butalbital, Aspirin, and Caffeine Capsules, USP. It is also not known whether Butalbital, Aspirin, and Caffeine Capsules, USP can cause fetal harm when administered to a pregnant woman or can affect reproduction capacity. Butalbital, Aspirin, and Caffeine Capsules, USP should be given to a pregnant woman only when clearly needed.

Nonteratogenic Effects:

Withdrawal seizures were reported in a two-day-old male infant whose mother had taken a butalbital-containing drug during the last 2 months of pregnancy. Butalbital was found in the infant’s serum. The infant was given phenobarbital 5 mg/kg, which was tapered without further seizure or other withdrawal symptoms.

Studies of aspirin use in pregnant women have not shown that aspirin increases the risk of abnormalities when administered during the first trimester of pregnancy. In controlled studies involving 41,337 pregnant women and their offspring, there was no evidence that aspirin taken during pregnancy caused stillbirth, neonatal death or reduced birth weight. In controlled studies of 50,282 pregnant women and their offspring, aspirin administration in moderate and heavy doses during the first four lunar months of pregnancy showed no teratogenic effect.

Therapeutic doses of aspirin in pregnant women close to term may cause bleeding in mother, fetus, or neonate. During the last 6 months of pregnancy, regular use of aspirin in high doses may prolong pregnancy and delivery.

Labor and Delivery

Ingestion of aspirin prior to delivery may prolong delivery or lead to bleeding in the mother or neonate.

Nursing Mothers

Aspirin, caffeine, and barbiturates are excreted in breast milk in small amounts, but the significance of their effects on nursing infants is not known. Because of potential for serious adverse reactions in nursing infants from Butalbital, Aspirin, and Caffeine Capsules, USP, a decision should be made whether to discontinue nursing or to discontinue the drug, taking into account the importance of the drug to the mother.

Pediatric Use

Safety and effectiveness in pediatric patients have not been established.

ADVERSE REACTIONS

The most frequent adverse reactions are drowsiness and dizziness. Less frequent adverse reactions are lightheadedness and gastrointestinal disturbances including nausea, vomiting, and flatulence. A single incidence of bone marrow suppression has been reported with the use of butalbital, aspirin, and caffeine capsules. Several cases of dermatological reactions including toxic epidermal necrolysis and erythema multiforme have been reported.

DRUG ABUSE AND DEPENDENCE

Controlled Substance

Butalbital, Aspirin, and Caffeine Capsules, USP is controlled by the Drug Enforcement Administration and is classified under Schedule III.

Abuse and Dependence

Butalbital
Barbiturates may be habit-forming: Tolerance, psychological dependence, and physical dependence may occur especially following prolonged use of high doses of barbiturates. The average daily dose for the barbiturate addict is usually about 1,500 mg. As tolerance to barbiturates develops, the amount needed to maintain the same level of intoxication increases; tolerance to a fatal dosage, however, does not increase more than two-fold. As this occurs, the margin between an intoxication dosage and fatal dosage becomes smaller. The lethal dose of a barbiturate is far less if alcohol is also ingested. Major withdrawal symptoms (convulsions and delirium) may occur within 16 hours and last up to 5 days after abrupt cessation of these drugs. Intensity of withdrawal symptoms gradually declines over a period of approximately 15 days. Treatment of barbiturate dependence consists of cautious and gradual withdrawal of the drug. Barbiturate-dependent patients can be withdrawn by using a number of different withdrawal regimens. One method involves initiating treatment at the patient’s regular dosage level and gradually decreasing the daily dosage as tolerated by the patient.

OVERDOSAGE

The toxic effects of acute overdosage of Butalbital, Aspirin, and Caffeine Capsules, USP are attributable mainly to its barbiturate component, and, to a lesser extent, aspirin. Because toxic effects of caffeine occur in very high dosages only, the possibility of significant caffeine toxicity from Butalbital, Aspirin, and Caffeine Capsules, USP overdosage is unlikely.

Signs and Symptoms

Symptoms attributable to acute barbiturate poisoning include drowsiness, confusion, and coma; respiratory depression; hypotension; hypovolemic shock. Symptoms attributable to acute aspirin poisoning include hyperpnea; acid-base disturbances with development of metabolic acidosis; vomiting and abdominal pain; tinnitus; hyperthermia; hypoprothrombinemia; restlessness; delirium; convulsions. Acute caffeine poisoning may cause insomnia, restlessness, tremor, and delirium; tachycardia and extrasystoles.

Treatment

Treatment consists primarily of management of barbiturate intoxication and the correction of the acid-base imbalance due to salicylism. Vomiting should be induced mechanically or with emetics in the conscious patient. Gastric lavage may be used if the pharyngeal and laryngeal reflexes are present and if less than 4 hours have elapsed since ingestion. A cuffed endotracheal tube should be inserted before gastric lavage of the unconscious patient and when necessary to provide assisted respiration. Diuresis, alkalinization of the urine, and correction of electrolyte disturbances should be accomplished through administration of intravenous fluids such as 1% sodium bicarbonate in 5% dextrose in water. Meticulous attention should be given to maintaining adequate pulmonary ventilation. The value of vasopressor agents such as Norepinephrine or Phenylephrine Hydrochloride in treating hypotension is questionable since they increase vasoconstriction and decrease blood flow. However, if prolonged support of blood pressure is required, Norepinephrine Bitartrate (Levophed®) may be given I.V. with the usual precautions and serial blood pressure monitoring. In severe cases of intoxication, peritoneal dialysis, hemodialysis, or exchange transfusion may be lifesaving. Hypoprothrombinemia should be treated with Vitamin K, intravenously.

Up-to-date information about the treatment of overdose can often be obtained from a Certified Regional Poison Control Center. Telephone numbers of Certified Regional Poison Control Centers are listed in the Physicians’ Desk Reference®.

Toxic and Lethal Doses (for adults)

Butalbital: toxic dose 1 g (20 capsules)
Aspirin: toxic blood level greater than 30 mg/100 mL; lethal dose 10-30 g
Caffeine: toxic dose 1 g (25 capsules)

DOSAGE AND ADMINISTRATION

One or 2 capsules every 4 hours. Total daily dose should not exceed 6 capsules. Extended and repeated use of this product is not recommended because of the potential for physical dependence.

HOW SUPPLIED

Butalbital, Aspirin, and Caffeine Capsules, USP
Green cap with a yellow body. Cap is imprinted with “WATSON” in red. Body is imprinted with “3219” in red. Bottles of 30 are supplied with child-resistant closures.

Store and Dispense
Below 25°C (77°F); tight container. Protect from moisture.

Rx only

Address medical inquiries to:
WATSON
Medical Communications
P.O. Box 1953
Morristown, NJ 07962-1953
800-272-5525

Watson Laboratories, Inc.
Corona, CA 92880 USA

Repackaged By :
Aidarex Pharmaceuticals LLC,
Corona, CA 92880

Revised: June 2009

190110
S0609

PRINCIPAL DISPLAY PANEL

Butalbital, Aspirin, and Caffeine Capsules, USP
NDC 33261-0922-30
30 Capsule Count Bottle Label